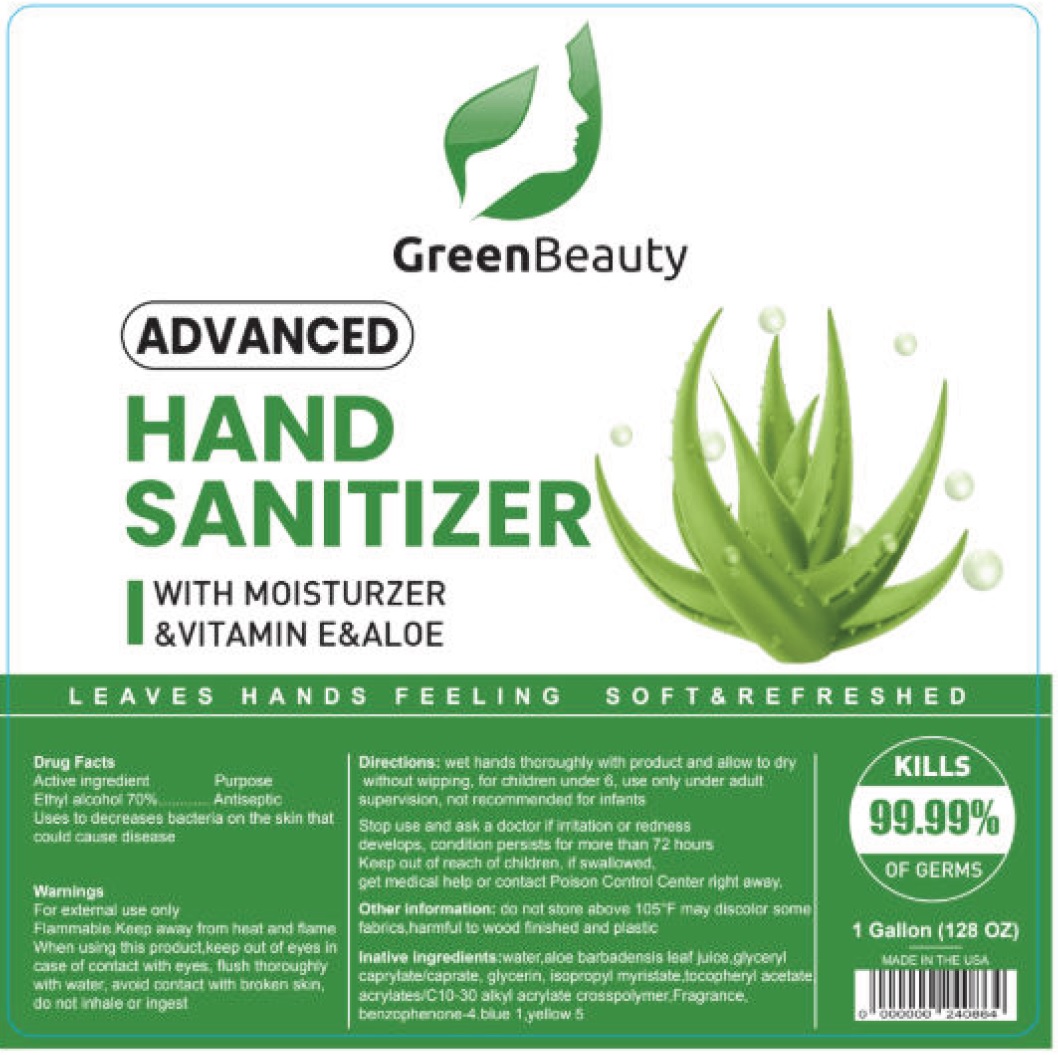 DRUG LABEL: Green Beauty Hand Sanitizer
NDC: 79347-000 | Form: GEL
Manufacturer: GTP International Corp
Category: otc | Type: HUMAN OTC DRUG LABEL
Date: 20221206

ACTIVE INGREDIENTS: ALCOHOL 0.7 mL/1 mL
INACTIVE INGREDIENTS: WATER; ALOE VERA LEAF; GLYCERYL MONOCAPRYLOCAPRATE; GLYCERIN; ISOPROPYL MYRISTATE; .ALPHA.-TOCOPHEROL ACETATE; CARBOMER INTERPOLYMER TYPE A (ALLYL SUCROSE CROSSLINKED); SULISOBENZONE; FD&C BLUE NO. 1; FD&C YELLOW NO. 5

Green Beauty Hand Sanitizer

Active ingredient

Ethyl alcohol 70%

Purpose

Antiseptic

Uses

to decreases bacteria on the skin that could cause disease

Warnings

For external use only

Flammable, Keep away from heat and flame.

When using this product,

keep out of eyes in case of contact with eyes, flush thoroughly with water, avoid contact with broken skin, do not inhale or ingest

Stop use and ask a doctor if

irritation or redness develops, condition persists for more than 72 hours

Keep out of reach of children.

If swallowed, get medical help or contact Poison Control Center right away.

Directions:

wet hands thoroughly with product and allow to dry without wipping, for children under 6, use only under adult supervision, not recommended for infants

Other information:

do nto store above 105°F may discolor some fabrics, harmful to wood finishes and plastic

Inactive Ingrediets:

water, aloe barbadensis leaf juice, glyceryl caprylate/caprate, glycerin, isopropyl myristate, tocopheryl acetate, acrylates/C10-30 alkyl acrylate crosspolymer, Fragrance. benzophennane-4, blue 1, yellow 5.